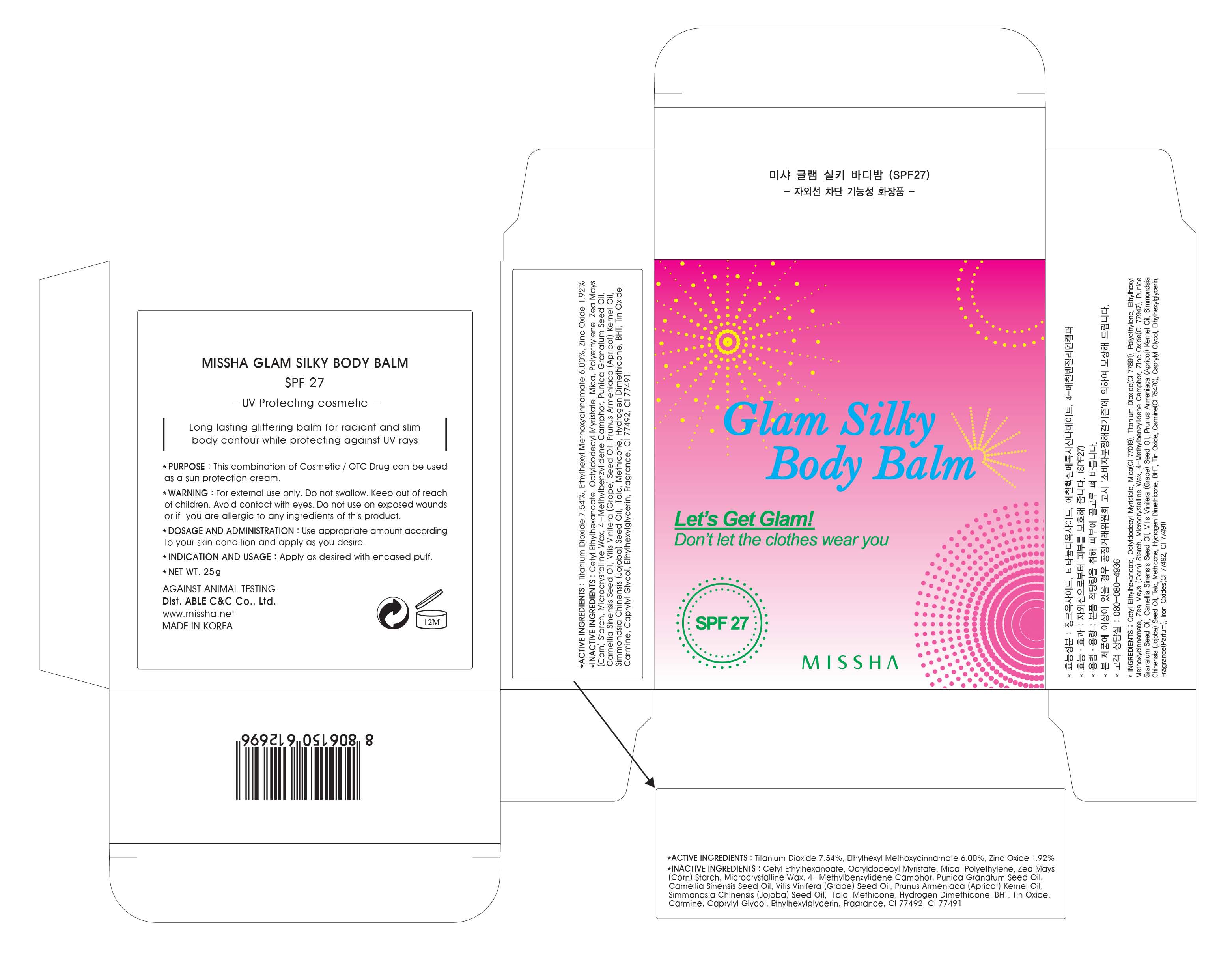 DRUG LABEL: MISSHA GLAM SILKY BODY BALM
NDC: 13733-016 | Form: CREAM
Manufacturer: ABLE C&C CO., LTD.
Category: otc | Type: HUMAN OTC DRUG LABEL
Date: 20121029

ACTIVE INGREDIENTS: Titanium Dioxide 1.88 g/25 g; OCTINOXATE 1.5 g/25 g; Zinc Oxide 0.48 g/25 g
INACTIVE INGREDIENTS: Cetyl Ethylhexanoate; Octyldodecyl Myristate; Mica; Talc

ACTIVE INGREDIENT

ACTIVE INGREDIENTS: Titanium Dioxide 7.54%, Ethylhexyl Methoxycinnamate 6.00%, Zinc Oxide 1.92%

INACTIVE INGREDIENT

INACTIVE INGREDIENTS:
Cetyl Ethylhexanoate, Octyldodecyl Myristate, Mica, Polyethylene, Zea Mays (Corn) Starch, Microcrystalline Wax, 4-Methylbenzylidene Camphor, Punica Granatum Seed Oil, Camellia Sinensis Seed Oil, Vitis Vinifera (Grape) Seed Oil, Prunus Armeniaca (Apricot) Kernel Oil, Simmondsia Chinensis (Jojoba) Seed Oil, Talc, Methicone, Hydrogen Dimethicone, BHT, Tin Oxide, Carmine, Caprylyl Glycol, Ethylhexylglycerin, Fragrance

PURPOSE

PURPOSE: This combination of Cosmetic / OTC Drug can be used as a sun protection cream

WARNINGS

WARNING:
For external use only.
Do not swallow.
Keep out of reach of children.
Avoid contact with eyes.
Do not use on exposed wounds or if you are allergic to any ingredients of this product.

KEEP OUT OF REACH OF CHILDREN

INDICATIONS AND USAGE

INDICATION AND USAGE: Apply as desired with encased puff.

DOSAGE AND ADMINISTRATION: Use appropriate amount according to your skin condition and apply as you desire.